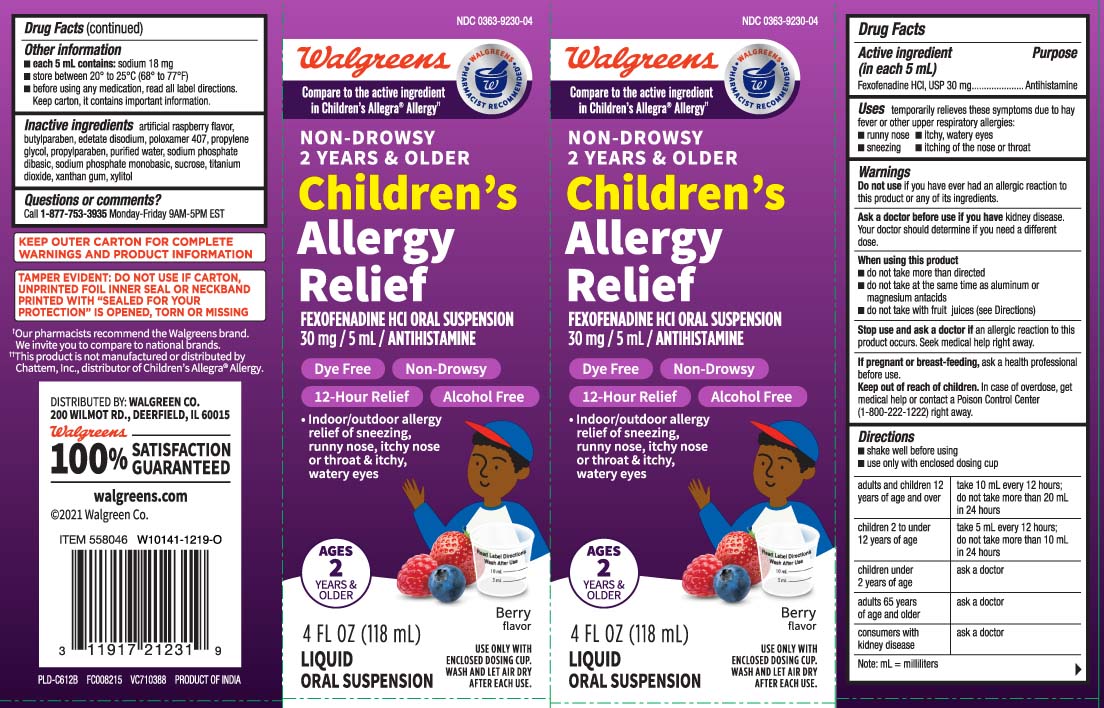 DRUG LABEL: Dye Free Wal Fex
NDC: 0363-9230 | Form: SUSPENSION
Manufacturer: Walgreens
Category: otc | Type: HUMAN OTC DRUG LABEL
Date: 20250902

ACTIVE INGREDIENTS: FEXOFENADINE HYDROCHLORIDE 30 mg/5 mL
INACTIVE INGREDIENTS: BUTYLPARABEN; EDETATE DISODIUM; POLOXAMER 407; PROPYLENE GLYCOL; PROPYLPARABEN; WATER; SODIUM PHOSPHATE, DIBASIC, ANHYDROUS; SODIUM PHOSPHATE, MONOBASIC, ANHYDROUS; SUCROSE; TITANIUM DIOXIDE; XANTHAN GUM; XYLITOL

DRUG FACTS

Active ingredient (in each 5 mL)

Fexofenadine HCL, USP 30 mg

Purpose

Antihistamine

Uses

temporarily relieves these symptoms due to hay fever or other upper respiratory allergies:

- runny nose
- sneezing
- itchy, watery eyes
- itching of the nose or throat

Warnings

Do not use

if you have ever had an allergic reaction to this product or any of its ingredients.

Ask a doctor before use if you have

kidney disease. Your doctor should determine if you need a different dose.

When using this product

- do not take more than directed
- do not take at the same time as aluminum or magnesium antacids
- do not take with fruit juices (see Directions)

Stop use and ask a doctor if

an allergic reaction to this product occurs. Seek medical help right away.

If pregnant or breast-feeding,

ask a health professional before use.

Keep out of reach of children.

In case of overdose, get medical help or contact a Poison Control Center (1-800-222-1222) right away.

Direction

- shake well before using
- use only with enclosed dosing cup

adults and children 12 years of age and over | take 10 mL every 12 hours; do not take more than 20 mL in 24 hours
children 2 to under 12 years of age | take 5 mL every 12 hours; do not take more than 10 mL in 24 hours
children under 2 years of age | ask a doctor
adults 65 years of age and older | ask a doctor
consumers with kidney disease | ask a doctor

Note: mL = milliliters

Other information

- each 5 mL contains: sodium 18 mg
- store between 20º to 25ºC (68º and 77ºF)
- before using any medication, read all label directions. Keep carton, it contains important information.

Inactive ingredients

artificial raspberry flavor, butylparaben, edetate disodium, poloxamer 407, propylene glycol, propylparaben, purified water, sodium phosphate dibasic, sodium phosphate monobasic, sucrose, titanium dioxide, xanthan gum, xylitol

Questions or comments?

Call 1-877-753-3935 Monday-Friday 9AM-5PM EST

Principal Display Panel

*Compare to the active ingredient in Children's Allegra® Allergy††

NON-DROWSY

2 YEARS & OLDER

Children's Allergy Relief

FEXOFENADINE HCl ORAL SUSPENSION

30 mg /PER 5 mL / ANTIHISTAMINE

- DYE FREE
- NON-DROWSY
- 12 - HOUR RELIEF
- ALCOHOL FREE
- Indoor/outdoor allergy relief of sneezing, runny nose itchy nose or throat & itchy, watery eyes

AGES 2 YEARS & OLDER

Berry Flavor

FL OZ (mL)

USE ONLY WITH ENCLOSED DOSING CUP.

WASH AND LET AIR DRY AFTER EACH USE

††This product is not manufactured or distributed by Chattem Inc., distributor of Children's Allegra® Allergy.

KEEP OUTER CARTON FOR COMPLETE WARNINGS AND PRODUCT INFORMATION

TAMPER EVIDENT: DO NOT USE IF CARTON, UNPRINTED FOIL INNER SEAL OR NECKBAND PRINTED WITH "SEAL FOR YOUR PROTECTION" IS OPENED, TORN OR MISSING

DISTRIBUTED BY: WALGREEN CO.

200 WILMOT RD., DEERFIELD, IL 60015

Product Label

WALGREENS Children's Allergy Relief Berry Flavor